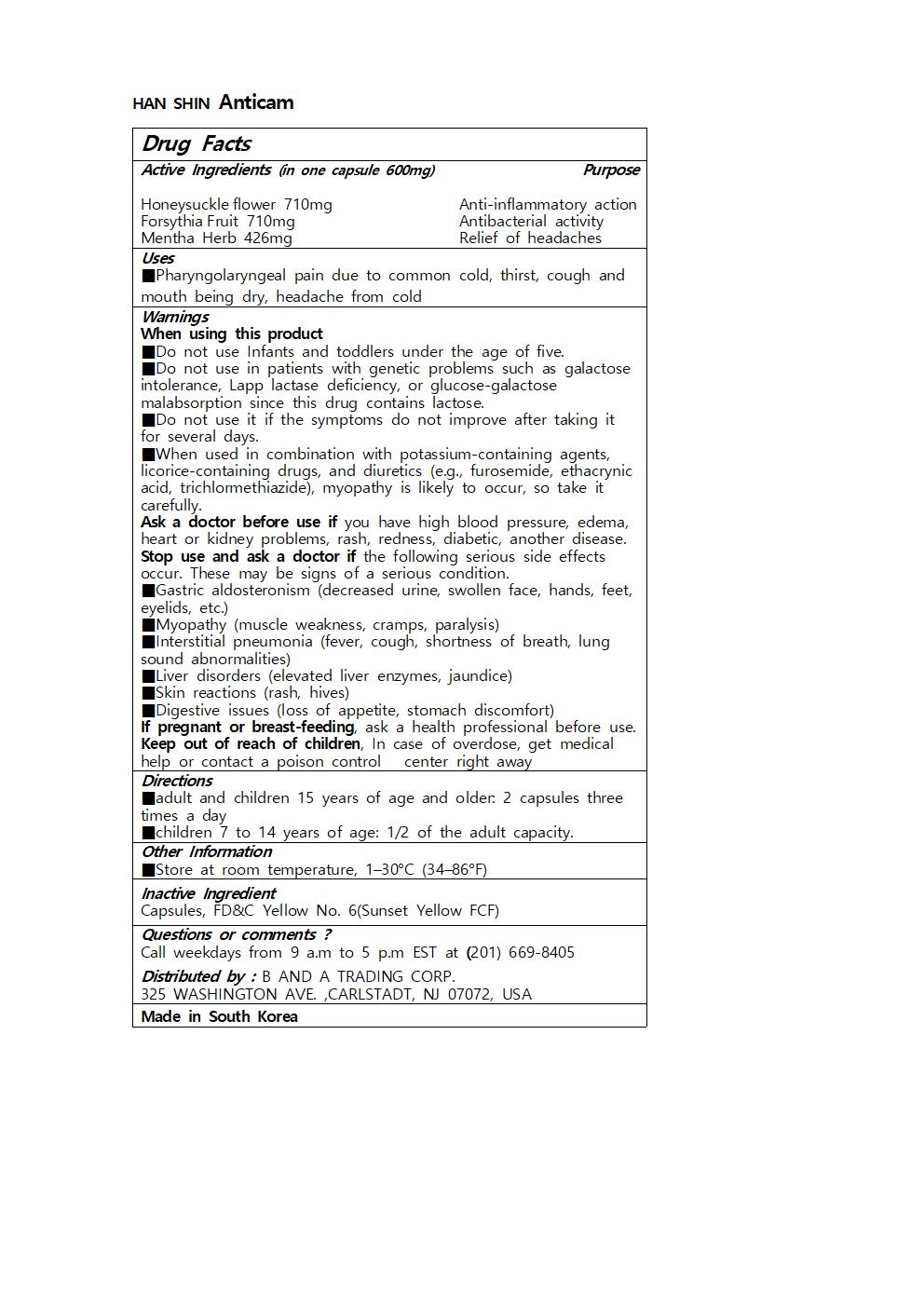 DRUG LABEL: HAN SHIN Anticam
NDC: 73466-0035 | Form: CAPSULE
Manufacturer: MISOCOS
Category: otc | Type: HUMAN OTC DRUG LABEL
Date: 20250301

ACTIVE INGREDIENTS: FORSYTHIA SUSPENSA FRUIT 710 mg/1 1; LONICERA HYPOGLAUCA FLOWER 710 mg/1 1
INACTIVE INGREDIENTS: FD&C YELLOW NO. 6; MENTHA ARVENSIS TOP

Drug Facts

ACTIVE INGREDIENT

Honeysuckleflower 710mg

ForsythiaFruit 710mg

Mentha Herb 426mg

INACTIVE INGREDIENT

Capsules, FD&C Yellow No. 6(Sunset Yellow FCF)

PURPOSE

■Pharyngolaryngeal pain due to common cold, thirst, cough and mouth being dry, headache from cold

keep out of reach of the children

INDICATIONS AND USAGE

■adult and children 15 years of age and older: 2 capsules three times a day

■children 7 to 14 years of age: 1/2 of the adult capacity.

Warnings

When using this product

■Do not use Infants and toddlers under the age of five.

■Do not use in patients with genetic problems such as galactose intolerance, Lapp lactase deficiency, or glucose-galactose malabsorption since this drug contains lactose.

■Do not use it if the symptoms do not improve after taking it for several days.

■When used in combination with potassium-containing agents, licorice-containing drugs, and diuretics (e.g., furosemide, ethacrynic acid, trichlormethiazide), myopathy is likely to occur, so take it carefully.

Ask a doctor before use if you have high blood pressure, edema, heart or kidney problems, rash, redness, diabetic, another disease.

Stop use and ask a doctor if the following serious side effects occur. These may be signs of a serious condition.

■Gastric aldosteronism (decreased urine, swollen face, hands, feet, eyelids, etc.)

■Myopathy (muscle weakness, cramps, paralysis)

■Interstitial pneumonia (fever, cough, shortness of breath, lung sound abnormalities)

■Liver disorders (elevated liver enzymes, jaundice)

■Skin reactions (rash, hives)

■Digestive issues (loss of appetite, stomach discomfort)

If pregnant or breast-feeding, ask a health professional before use.

Keep out of reach of children, In case of overdose, get medical help or contact a poison control center right away

DOSAGE AND ADMINISTRATION

for oral use only